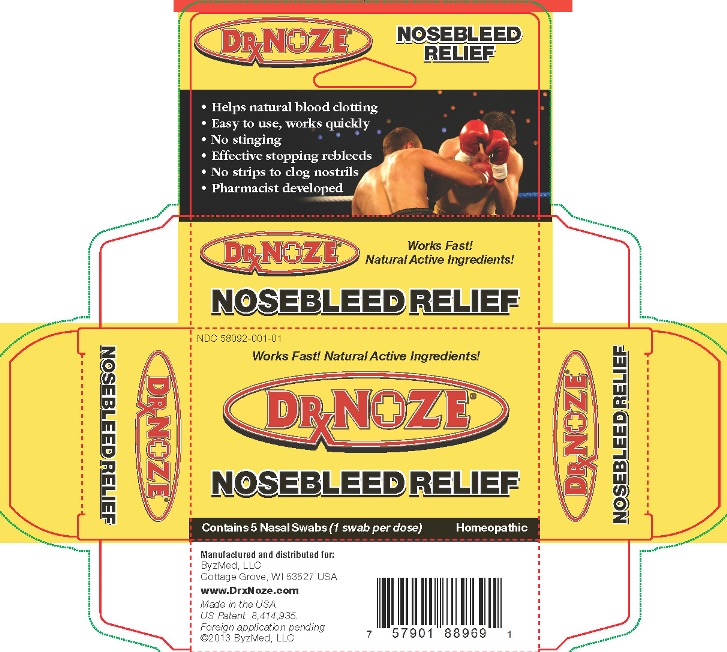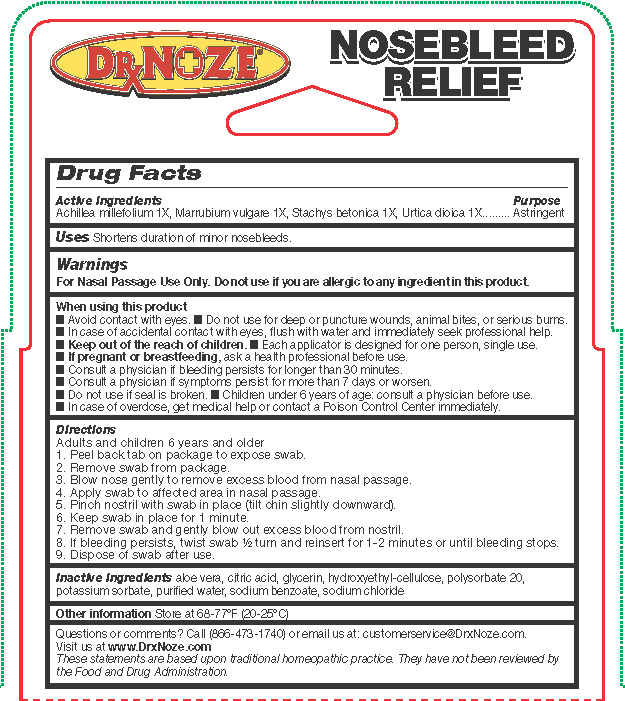 DRUG LABEL: DrxNoze Nosebleed Relief
NDC: 58092-001 | Form: SWAB
Manufacturer: ByzMed, LLC
Category: homeopathic | Type: HUMAN OTC DRUG LABEL
Date: 20140131

ACTIVE INGREDIENTS: ACHILLEA MILLEFOLIUM 1 [hp_X]/1.5 mL; MARRUBIUM VULGARE 1 [hp_X]/1.5 mL; STACHYS OFFICINALIS 1 [hp_X]/1.5 mL; URTICA DIOICA 1 [hp_X]/1.5 mL
INACTIVE INGREDIENTS: ALOE VERA LEAF; CITRIC ACID MONOHYDRATE; GLYCERIN; HYDROXYETHYL CELLULOSE (100 MPA.S AT 2%); POLYSORBATE 20; POTASSIUM SORBATE; WATER; SODIUM BENZOATE; SODIUM CHLORIDE

DrxNoze® Nosebleed Relief Drug Facts

Active ingredients

Achillea millefolium 1X, Marrubium vulgare 1X, Stachys betonica 1X, Urtica dioica 1X

Purpose

Astringent

Keep Out of Reach of Children

Keep out of the reach of children.

Uses

Shortens duration of minor nose bleeds.

Warnings

For Nasal Passage Use Only. Do not use if you are allergic to any ingredient in this product.

When using this product

- Avoid contact with eyes.
- Do not use for deep or puncture wounds, animal bites, or serious burns.
- In case of accidental contact with eyes, flush with water and immediately seek professional help.
- Keep out of the reach of children.
- Each applicator is designed for one person, single use.
- If pregnant or breastfeeding, ask a health professional before use.
- Consult a physician if bleeding persists for longer than 30 minutes.
- Consult a physician if symptoms persist for more than 7 days or worsen.
- Do not use if seal is broken.
- Children under 6 years of age: consult a physician before use.
- In case of overdose, get medical help or contact a Poison Control Center immediately.

Directions

Adults and children 6 years and older:
1. Peel back tab on package to expose swab.
2. Remove swab from package.
3. Blow nose gently to remove excess blood from nasal passage.
4. Apply swab to affected area in nasal passage.
5. Pinch nostril with swab in place (tilt chin slightly downward).
6. Keep swab in place for 1 minute.
7. Remove swab and gently blow out excess blood from nostril.
8. If bleeding persists, twist swab ½ turn and reinsert for 1-2 minutes or until bleeding stops.
9. Dispose of swab after use.

Inactive Ingredients

aloe vera, citric acid, glycerin, hydroxyethyl-cellulose, polysorbate 20, potassium sorbate, purified water, sodium benzoate, sodium chloride

Other Information

Store at 68-77°F (20-25°C)

Package/Label Principal Display Panel

DRxNOZE® NOSEBLEED RELIEF

Works Fast! Natural Active Ingredients!

- Helps natural blood clotting
- Easy to use, works quickly
- No stinging
- Effective stopping rebleeds
- No strips to clog nostrils
- Pharmacist developed

Contains 5 Nasal Swabs (1 swab per dose)

Homeopathic

Manufactured and distributed for:

ByzMed, LLC

Cottage Grove, WI 53527 USA

www.DrxNoze.com

Made in the USA

US Patent 8,414,935

Foreign application pending

©2013 Byzmed, LLC

Questions or comments? Call (866-473-1740) or email us at: customerservice@DrxNoze.com.

Visit us at www.DrxNoze.com

These statements are based upon traditional homeopathic practice. They have not been reviewed by the Food and Drug Administration.

Carton Label – Front

Carton Label – Back